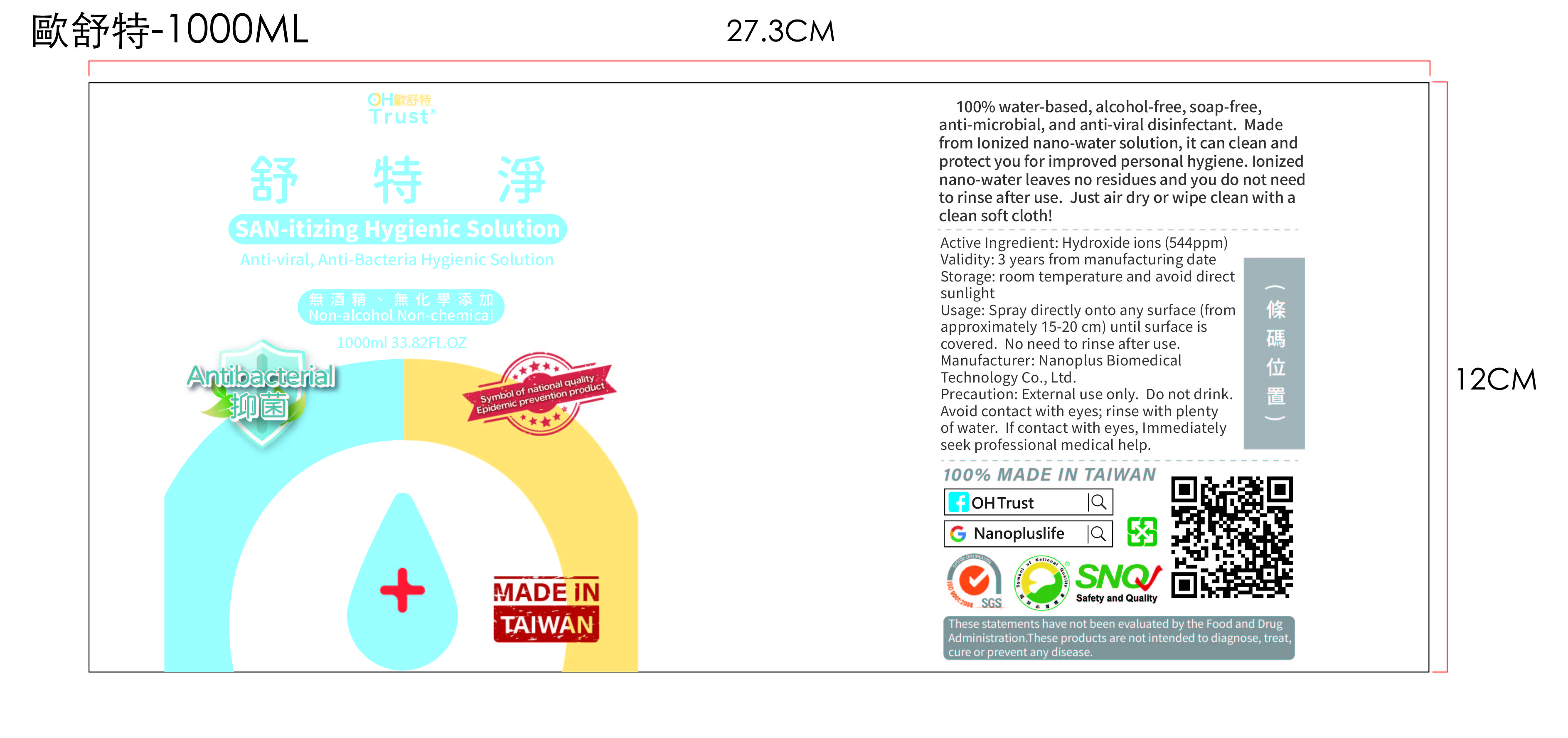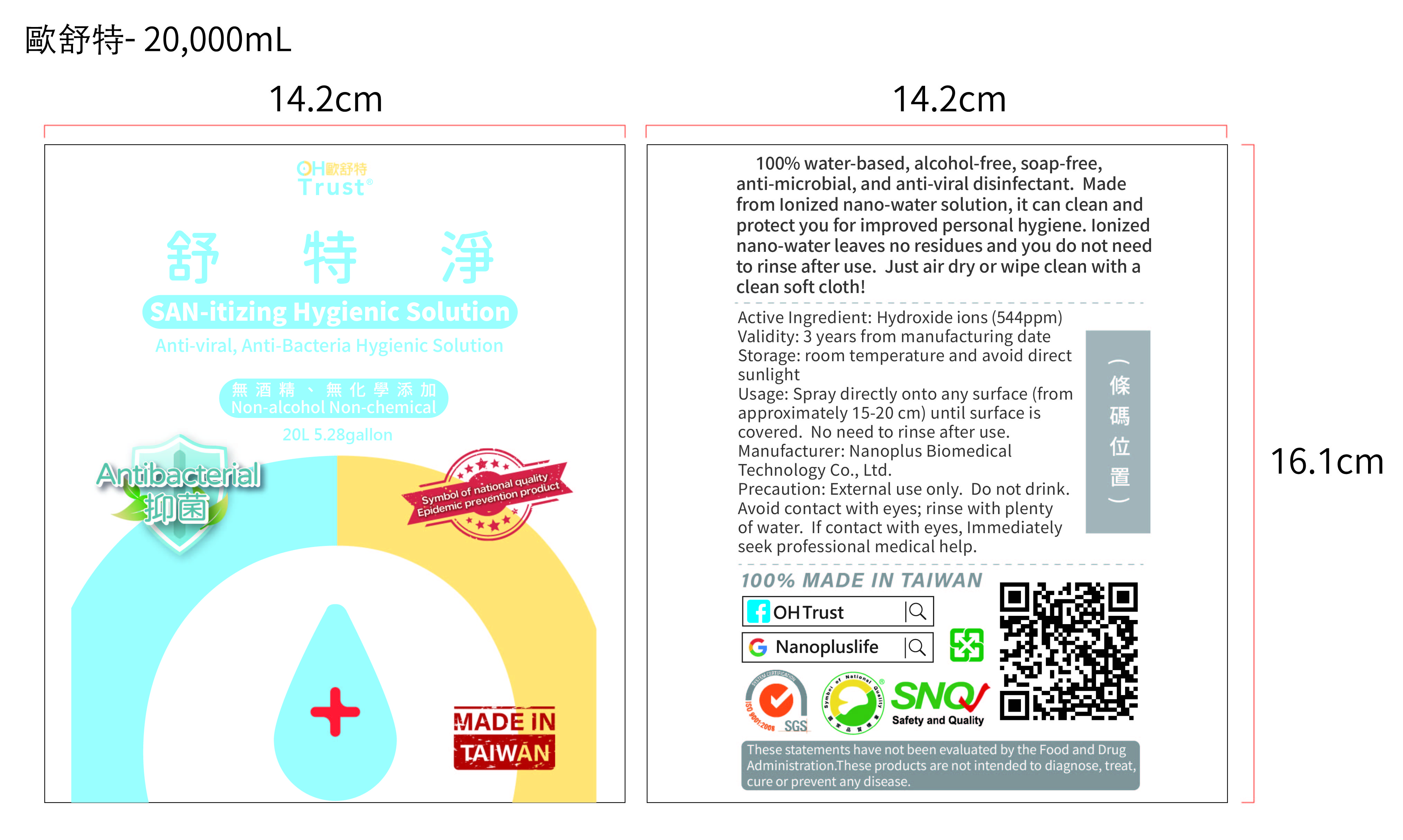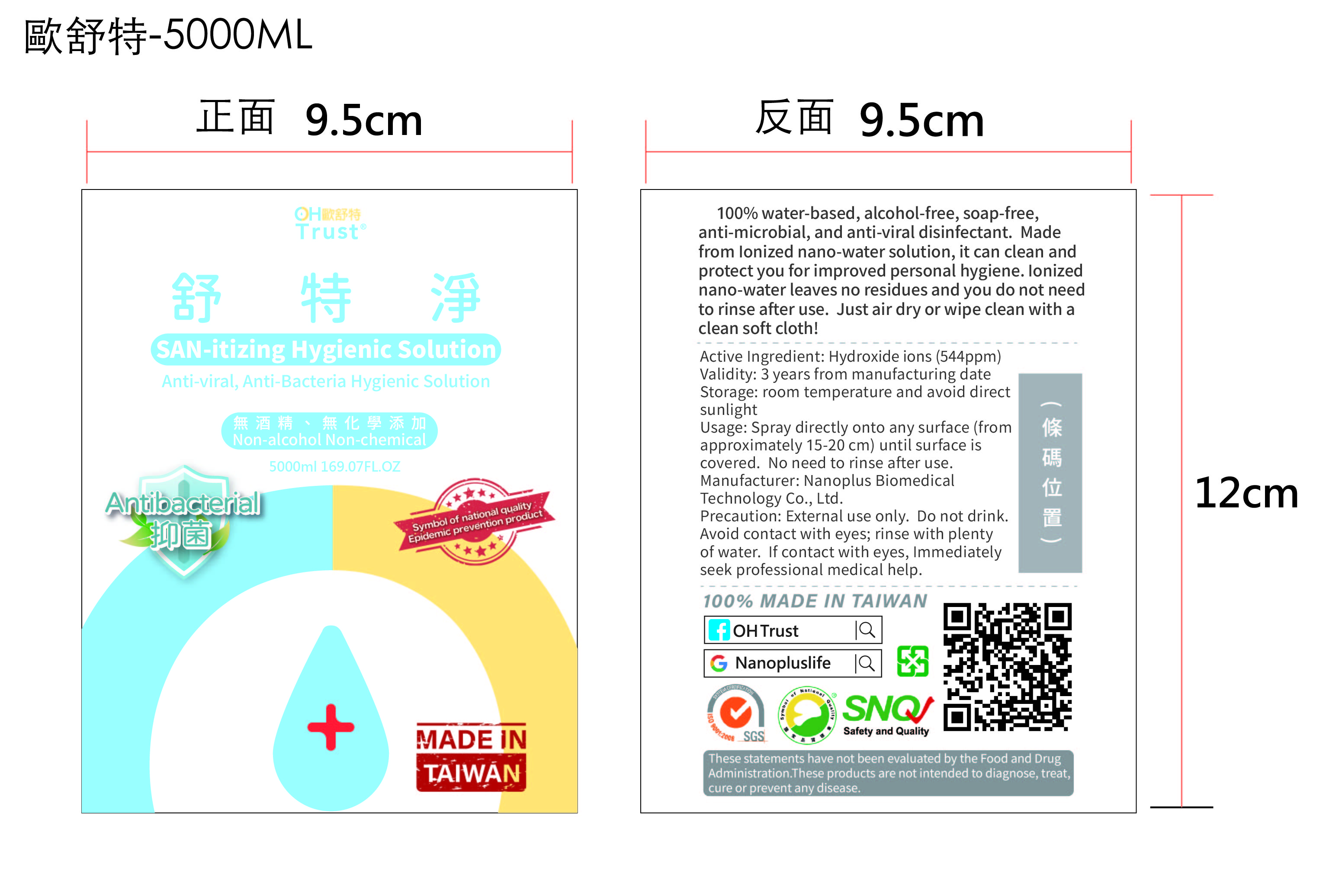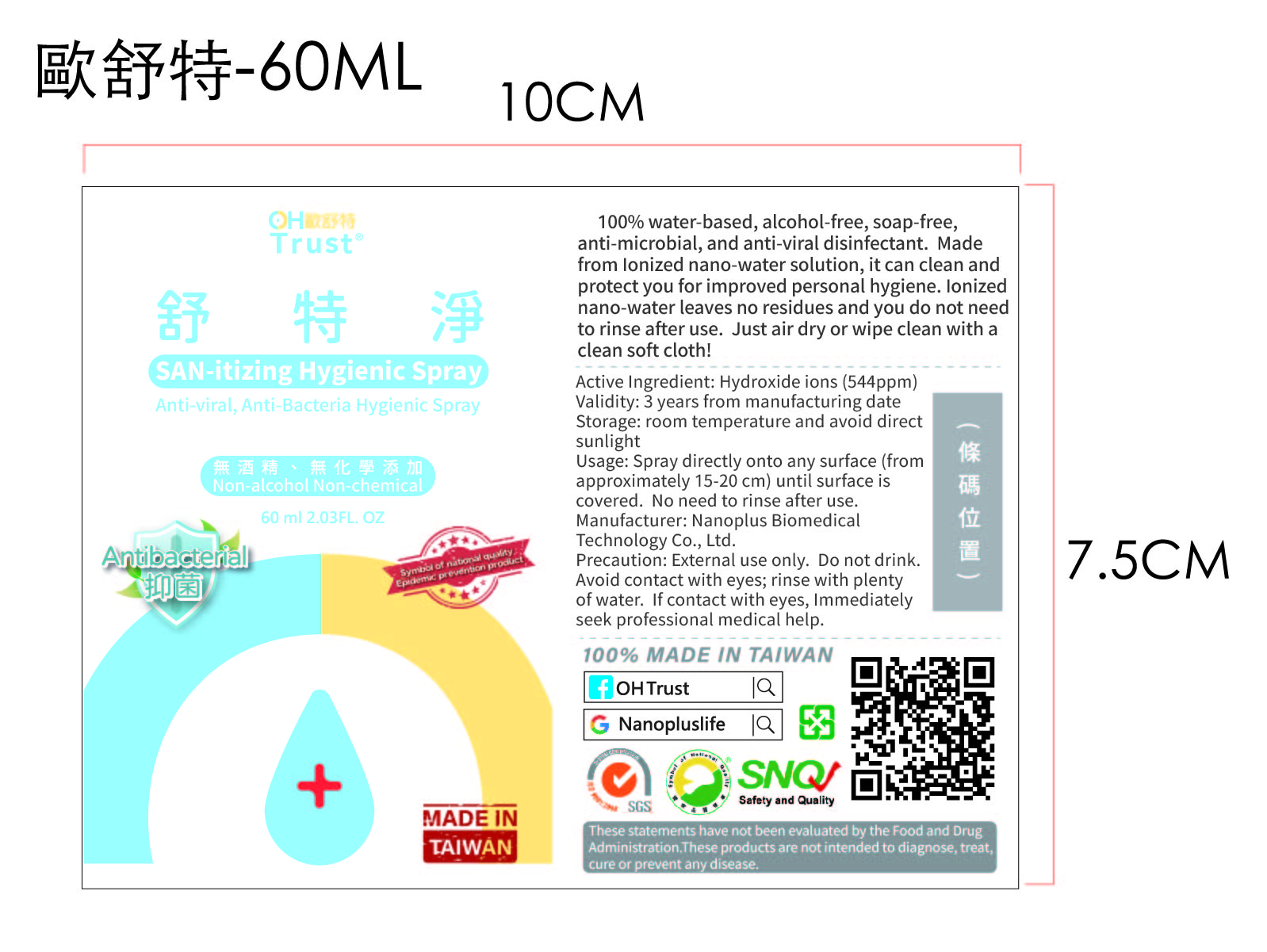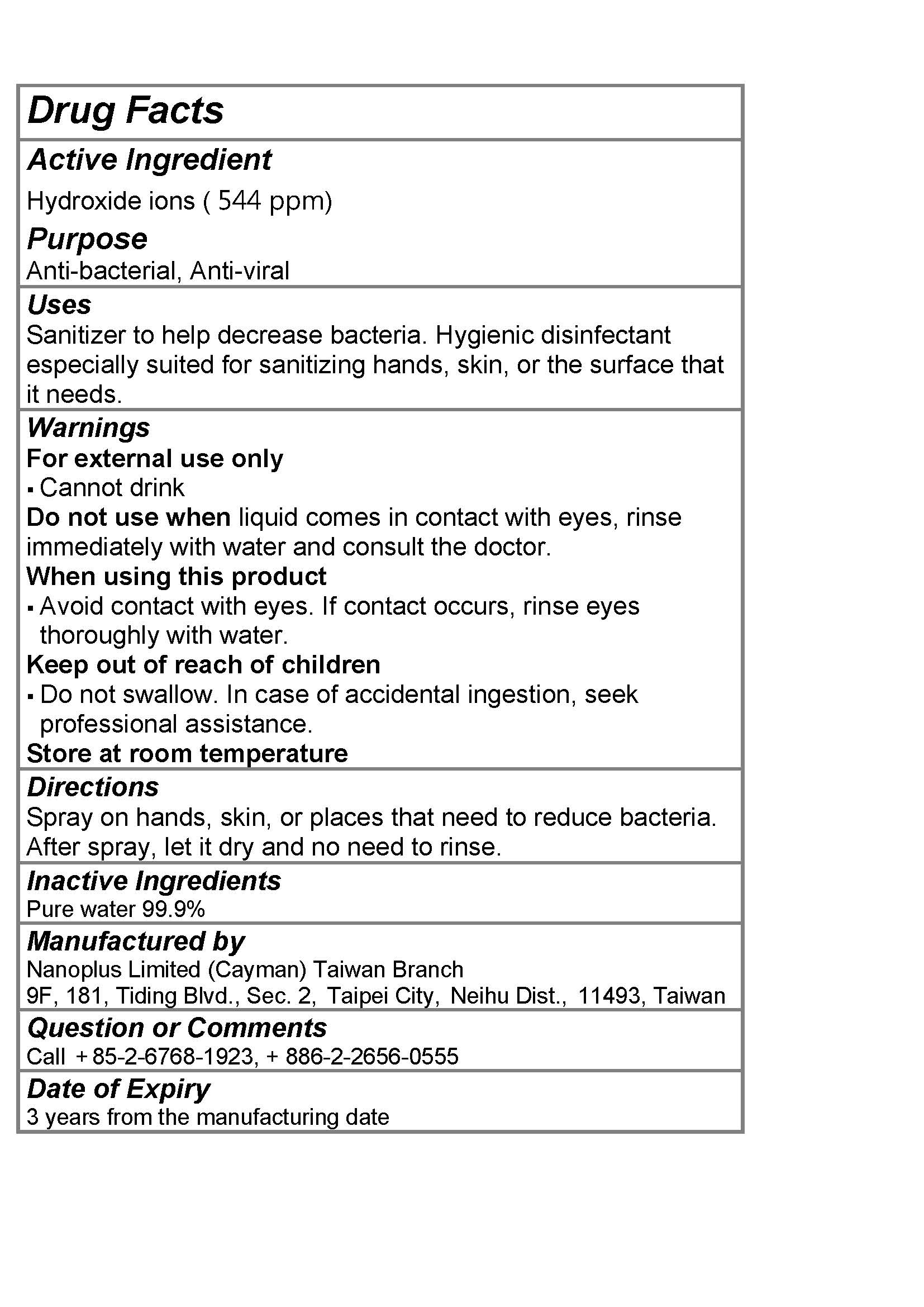 DRUG LABEL: OHTrust Nano Ion Water
NDC: 70970-006 | Form: LIQUID
Manufacturer: Nanoplus Limited (Cayman) Taiwan Branch
Category: otc | Type: HUMAN OTC DRUG LABEL
Date: 20250210

ACTIVE INGREDIENTS: HYDROXIDE ION 0.2 g/100 mL
INACTIVE INGREDIENTS: WATER

Nanoplus 006-01, 02, 03, 04, 05

Active Ingredient(s)

Hydroxide ions (544ppm)

Purpose

Anti-bacterial, Anti-viral

Use

Sanitizer to help decrease bacteria. Hygienic disinfectant especially suited for sanitizing hands, skin, or the surface that it needs.

Warnings

For external use only. Cannot drink

Do not use when liquid comes in contact with eyes, rinse immediately with water and consult the doctor

When using this product avoid contact with eyes. If contact occurs, rinse eyes thoroughly with water

.

Keep out of reach of children

Do not swallow. In case of accidental ingestion, seek professional assistance.

Directions

- Spray on hands, skin, or places that need to reduce bacteria. After spray, let it dry and no need to rinse.

Other information

- Store at room temperature

Inactive ingredients

Pure Water 99.9%

Package Label - Principal Display Panel

60 mL NDC: 70970-006-01

1000 mL NDC: 70970-006-02

5000 mL NDC: 70970-006-03

20000 mL NDC: 70970-006-04